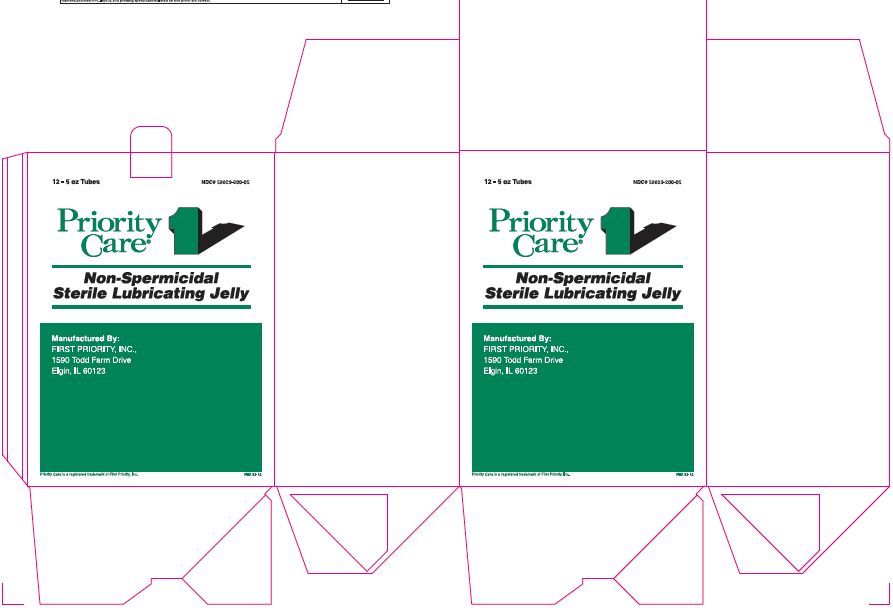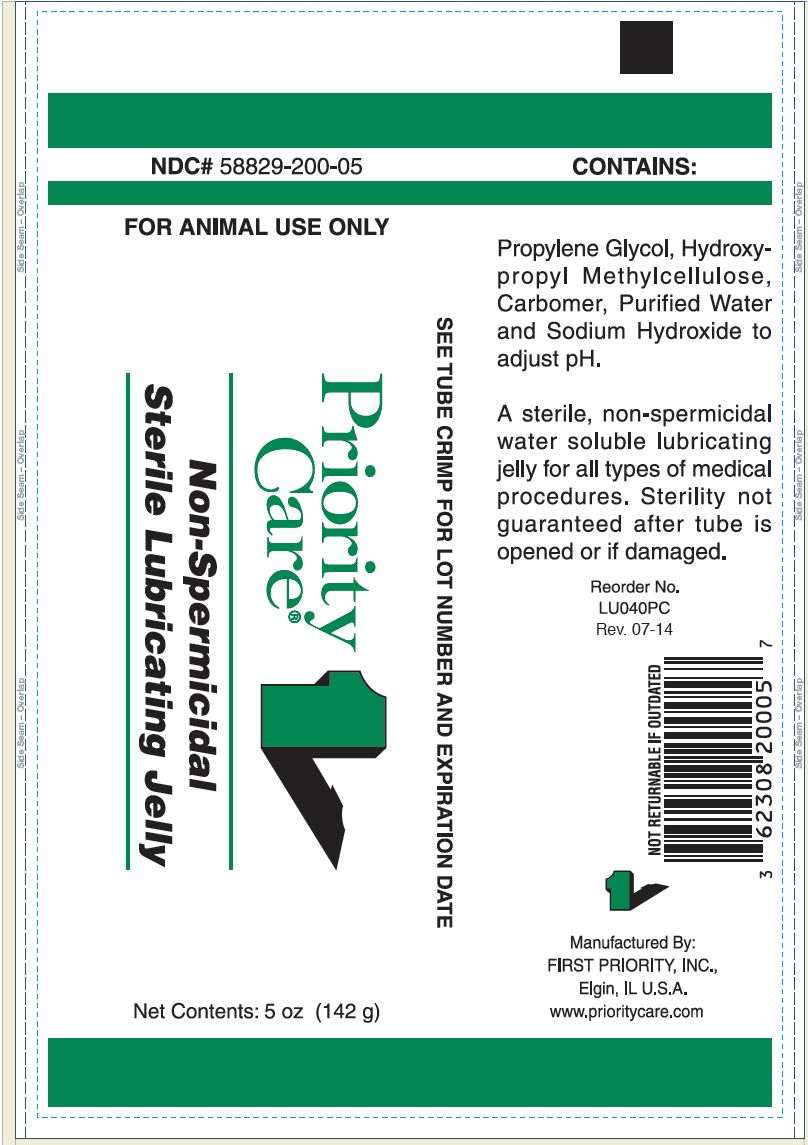 DRUG LABEL: Non Spermicidal Sterile Lubricating Jelly
NDC: 58829-200 | Form: JELLY
Manufacturer: FIRST PRIORITY INCORPORATED
Category: animal | Type: OTC ANIMAL DRUG LABEL
Date: 20241028

ACTIVE INGREDIENTS: PROPYLENE GLYCOL 15580 mg/1 g

Non-Spermicidal Sterile Lubricating Jelly

WHEN USING

FOR ANIMAL USE ONLY

INDICATIONS AND USAGE

A sterile, non-spermicidal water soluble lubricating jelly for all types of medical procedures. Sterility not guaranteed after tube is opened or if damaged.

CONTAINS:

Propylene Glycol, Hydroxypropyl Methylcellulose, Carbomer, Purified Water and Sodium Hydroxide to adjust pH.

Net Contents:

5 oz (142 g) Reorder No. LU040PC

INFORMATION FOR OWNERS/CAREGIVERS

Manufactured By: FIRST PRIORITY, INC., ELGIN, IL U.S.A

www.prioritycare.com

NOT RETURNABLE IF OUTDATED

SEE TRUBE CRIMP FOR LOT NUBMER AND EXPIRATION DATE